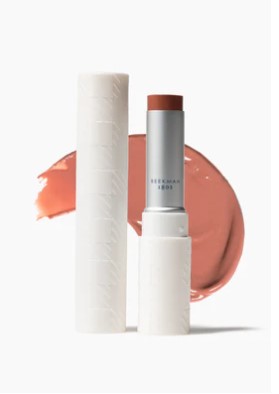 DRUG LABEL: Tinted Lip Cream SPF 15
NDC: 68577-169 | Form: CREAM
Manufacturer: COSMAX USA, CORPORATION
Category: otc | Type: HUMAN OTC DRUG LABEL
Date: 20241218

ACTIVE INGREDIENTS: ZINC OXIDE 9.28 mg/100 mg
INACTIVE INGREDIENTS: POLYGLYCERYL-4 ISOSTEARATE; STEARALKONIUM HECTORITE; PROPYLENE CARBONATE; KAOLIN; DEHYDROACETIC ACID; DIMER DILINOLEYL DIMER DILINOLEATE; DIGLYCERYL SEBACATE/ISOPALMITATE; TRIDECYL TRIMELLITATE; GOAT MILK; POLYGLYCERYL-3 PENTARICINOLEATE; POLYHYDROXYSTEARIC ACID (2300 MW); TOCOPHEROL; CORN OIL; SYNTHETIC WAX (540 MW); HYDROGENATED POLYDECENE (1500 CST); CERESIN; QUERCETIN; LECITHIN, SUNFLOWER; IRON OXIDES; BIS-DIGLYCERYL POLYACYLADIPATE-2; PENTAERYTHRITYL TETRAISOSTEARATE; DIISOSTEARYL MALATE; BUTYLOCTYL SALICYLATE; CAPRYLIC/CAPRIC TRIGLYCERIDE; ETHYLHEXYL PALMITATE; SILICA; BEHENYL ACRYLATE POLYMER; ISOSTEARIC ACID; POLYGLYCERYL-2 TRIISOSTEARATE; TITANIUM DIOXIDE

BEEKMAN SPF 15 GOAT MILK TINTED LIP CREAM SPICY NUDEY

Active ingredient

Zinc Oxide 9.82%

Purpose

Sunscreen

USES

- helps prevent sunburn
- If used as directed with other sun protection measures (see Directions), decreases the risk of skin cancer and early skin aging caused by the sun.

Warnings

For external use only

Do not useon damaged or broken skin

Keep out of reach of children. If swallowed, get medical help or contact a Poison Control Center right away.

DIRECTIONS

- Apply liberally 15 minutes before sun exposure
- Reapply:
  - use a water resistant sunscreen if swimming or sweating
  - at least every 2 hours
- Children under 6 months: Ask a doctor
- Sun Protection Measures: Spending time in the sun increases your risk of skin cancer and early skin aging.
  To decrease the risk, regularly use a sunscreen with Broad Spectrum SPF of 15 or higher and other sun protection measures including:
  - Limit time in the sun, especially from 10a.m.- 2p.m.
  - Wear long-sleeved shirts, pants, hats and sunglasses

Inactive ingredients:

Hydrogenated Polydecene, Diisostearyl Malate, Ozokerite, Synthetic Wax, Caprylic/Capric Triglyceride, Ethylhexyl Palmitate, Butyloctyl Salicylate, Tridecyl Trimellitate, Bis-Diglyceryl Polyacyladipate-2, Pentaerylhrityl Tetraisostearate, Polyglyceryl-4 Isostearate, Dimer Dilinoleyl Dimer Dilinoleate, Diglyceryl Sebacate/lsopalmitate*, Moringa Oil/Hydrogenated Moringa Oil Esters, Polyhydroxystearic Acid, Silica, Caprae Lac (Goat Milk), Tocopherol (Vitamin E), Kaolin, Hydrogenated Vegetable Oil, Quercetin, Oleic/Linoleic/Linolenic Polyglycerides, Poly C10-30 Alkyl Acrylate, Isostearic Acid, Lecithin, Polyglyceryl-3 Polyricinoleate, Polyglyceryl-2 Triisostearate, Stearalkonium Hectorite, Propylene Carbonate, Dehydroacetic Acid, Iron Oxides (CI 77491), Iron Oxides (CI 77499), Iron Oxides (CI 77492), Titanium Dioxide (CI 77891), Carmine (CI 75470).